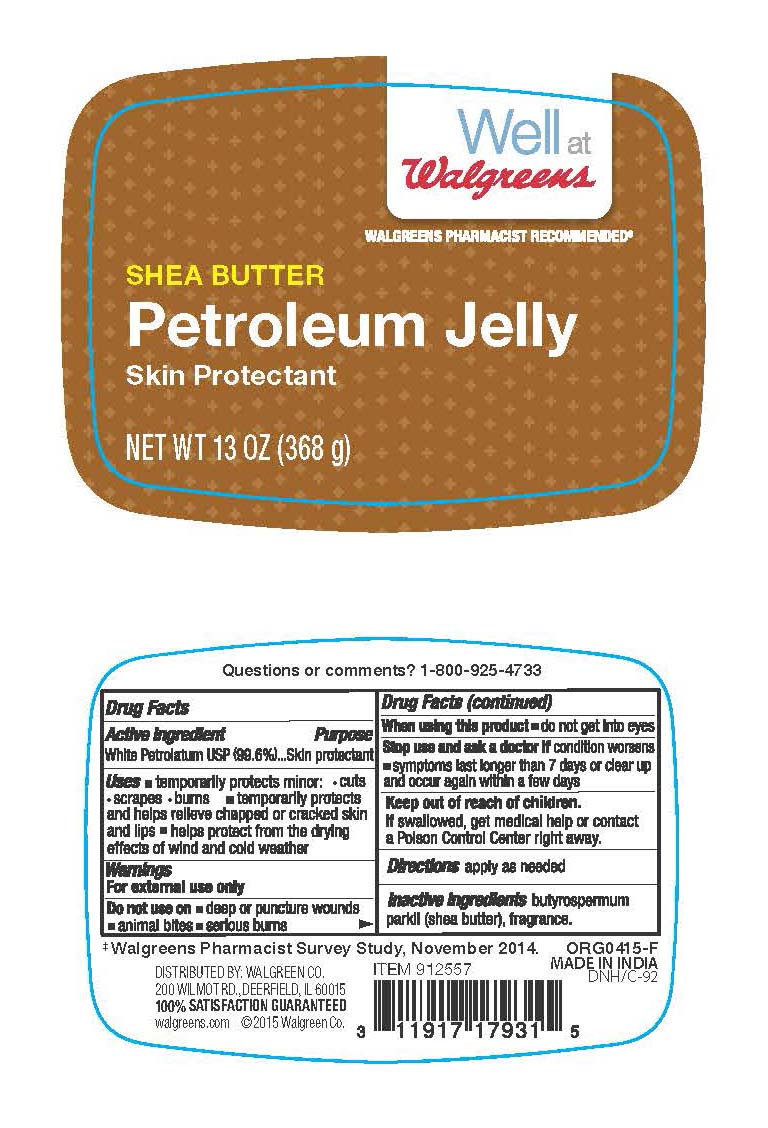 DRUG LABEL: Shea Butter Petroleum Jelly
NDC: 0363-0740 | Form: JELLY
Manufacturer: Walgreens
Category: otc | Type: HUMAN OTC DRUG LABEL
Date: 20241217

ACTIVE INGREDIENTS: PETROLATUM 99.6 g/100 g
INACTIVE INGREDIENTS: SHEA BUTTER 0.1 g/100 g

Active Ingredient

White Petrolatum USP (99.6%)

Purpose

Skin Protectant

Uses

temporarily protects minor: cuts, scrapes, burns; temporarily protects and helps relieve chapped or cracked skin and lips; helps protect from the drying effects of wind and cold weather

Warnings

For external use only

When using this product

do not get into eyes

Stop use and ask a doctor if

condition worsens, symptoms last longer than 7 days or clear up and occur again within a few days

Do not use on

deep or puncture wounds, animal bites, serious burns

Keep out of reach of children.

If swallowed, get medical help or contact a Poison Control Center right away.

Directions

apply as needed

Inactive ingredients

butyrospermum parkii (shea butter), fragrance

Questions or comments?

1-800-925-4733